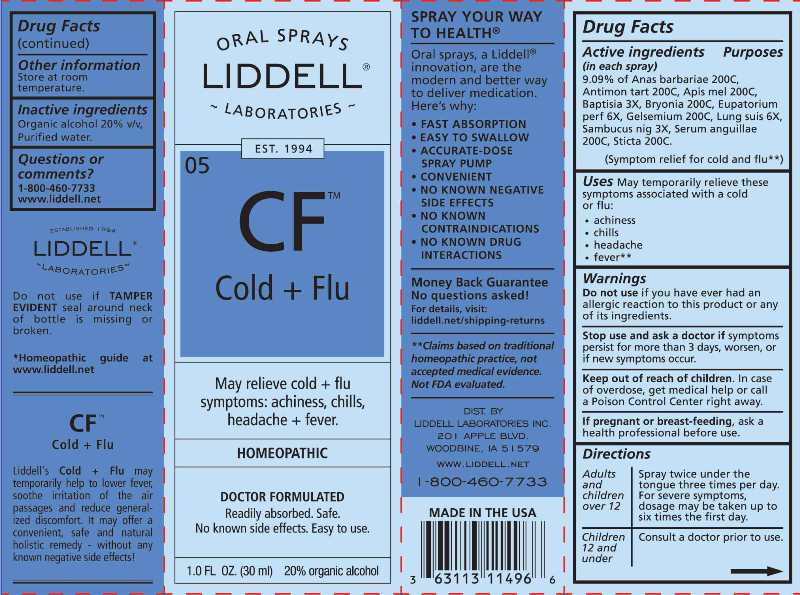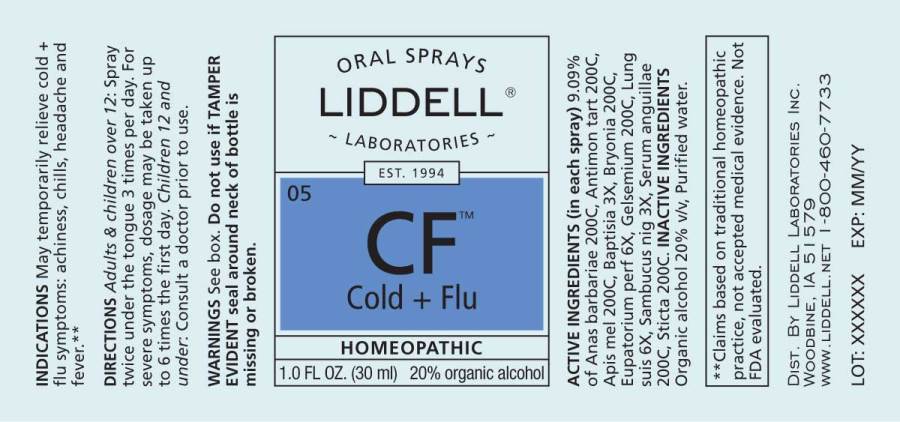 DRUG LABEL: Cold plus Flu
NDC: 50845-0247 | Form: SPRAY
Manufacturer: Liddell Laboratories, Inc.
Category: homeopathic | Type: HUMAN OTC DRUG LABEL
Date: 20240701

ACTIVE INGREDIENTS: CAIRINA MOSCHATA HEART/LIVER AUTOLYSATE 200 [hp_C]/1 mL; ANTIMONY POTASSIUM TARTRATE 200 [hp_C]/1 mL; APIS MELLIFERA 200 [hp_C]/1 mL; BAPTISIA TINCTORIA ROOT 3 [hp_X]/1 mL; BRYONIA ALBA ROOT 200 [hp_C]/1 mL; EUPATORIUM PERFOLIATUM FLOWERING TOP 6 [hp_X]/1 mL; GELSEMIUM SEMPERVIRENS ROOT 200 [hp_C]/1 mL; SUS SCROFA LUNG 6 [hp_X]/1 mL; SAMBUCUS NIGRA FLOWERING TOP 3 [hp_X]/1 mL; ANGUILLA ROSTRATA BLOOD SERUM 200 [hp_C]/1 mL; LOBARIA PULMONARIA 200 [hp_C]/1 mL
INACTIVE INGREDIENTS: WATER; ALCOHOL

DRUG FACTS:

ACTIVE INGREDIENTS:

(in each drop) 9.09% of Anas Barbariae, Hepatis Et Cordis Extractum 200C, Antimonium Tartaricum 200C, Apis Mellifica 200C, Baptisia Tinctoria 3X, Bryonia (Alba) 200C, Eupatorium Perfoliatum 6X, Gelsemium Sempervirens 200C, Lung Suis 6X, Sambucus Nigra 3X, Serum Anguillae 200C, Sticta Pulmonaria 200C.

USES:

May temporarily relieve cold + flu symptoms:

• achiness

• chills

• headache

• fever**

(Symptom relief for cold and flu**)

WARNINGS:

Do not use if you have ever had an allergic reaction to this product or any of its ingredients.

Stop use and ask a doctor if symptoms persist for more than 3 days, worsen, or if new symptoms occur.

Keep out of reach of children. In case of overdose, get medical help or call a Poison Control Center right away.

If pregnant or breast-feeding, ask a health professional before use.

Do not use if TAMPER EVIDENT seal around neck of bottle is missing or broken.

Keep out of reach of children. In case of overdose, get medical help or call a Poison Control Center right away.

DIRECTIONS:

Adults and children over 12: Spray twice under the tongue three times per day. For severe symptoms, dosage may be taken up to six times the first day.

Children 12 and under: Consult a doctor prior to use.

Store at room temperature.

INDICATIONS:

May temporarily relieve cold + flu symptoms:

• achiness

• chills

• headache

• fever**

(Symptom relief for cold and flu**)

**Claims based on traditional homeopathic practice, not accepted medical evidence. Not FDA evaluated.

INACTIVE INGREDIENTS:

Organic alcohol 20% v/v, Purified water

QUESTIONS:

DIST. BY

LIDDELL LABORATORIES INC.

201 APPLE BLVD.

WOODBINE, IA 51579

WWW.LIDDELL.NET

1-800-460-7733

PACKAGE LABEL DISPLAY:

ORAL SPRAYS

LIDDELL

LABORATORIES

EST. 1994

^05CF

Cold + Flu

May relieve cold + flu

symptoms: achiness, chills,

headache + fever.

HOMEOPATHIC

DOCTOR FORMULATED

Readily absorbed. Safe.

No known side effects. Easy to use.

1.0 FL OZ. (30 ml)